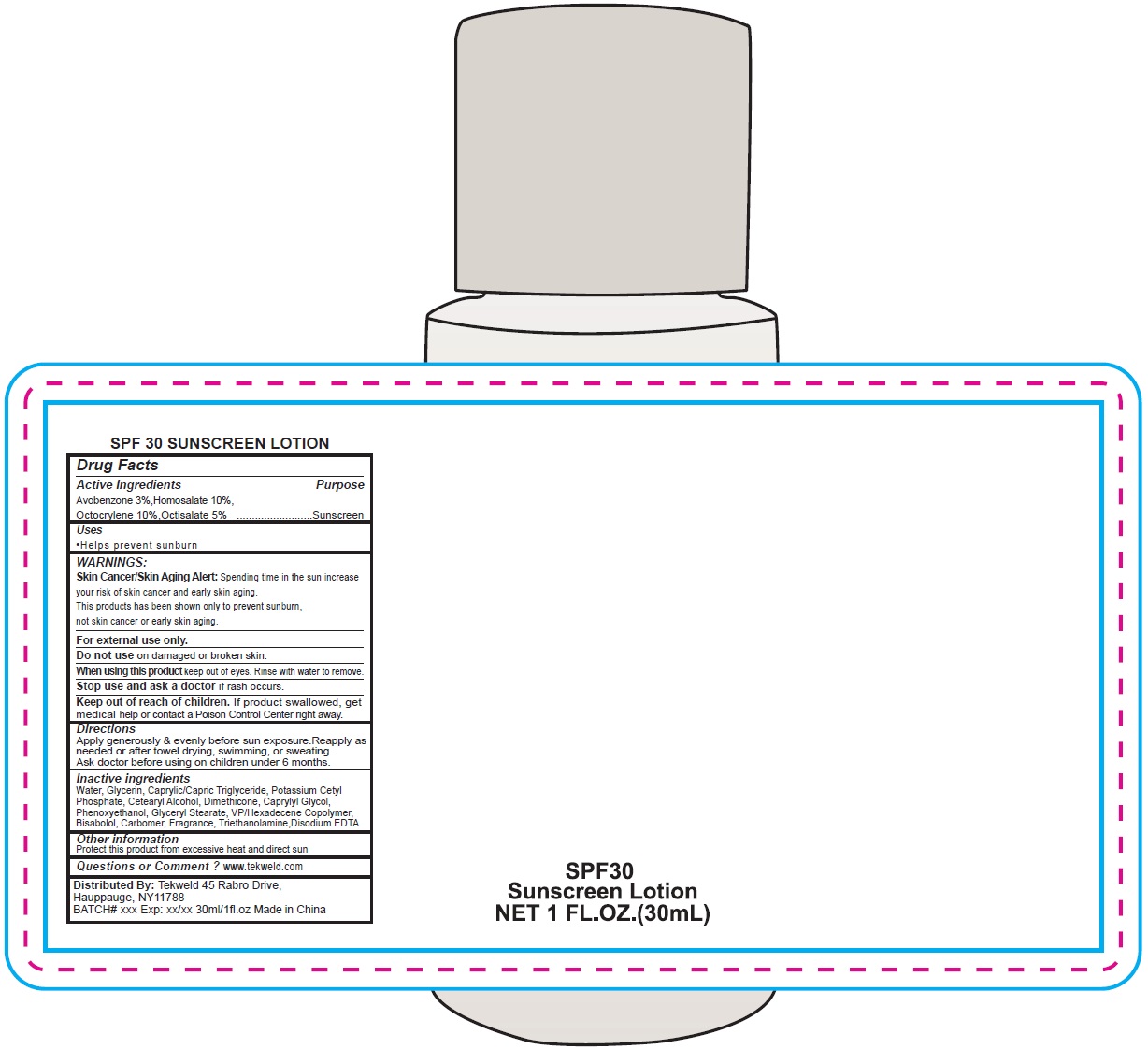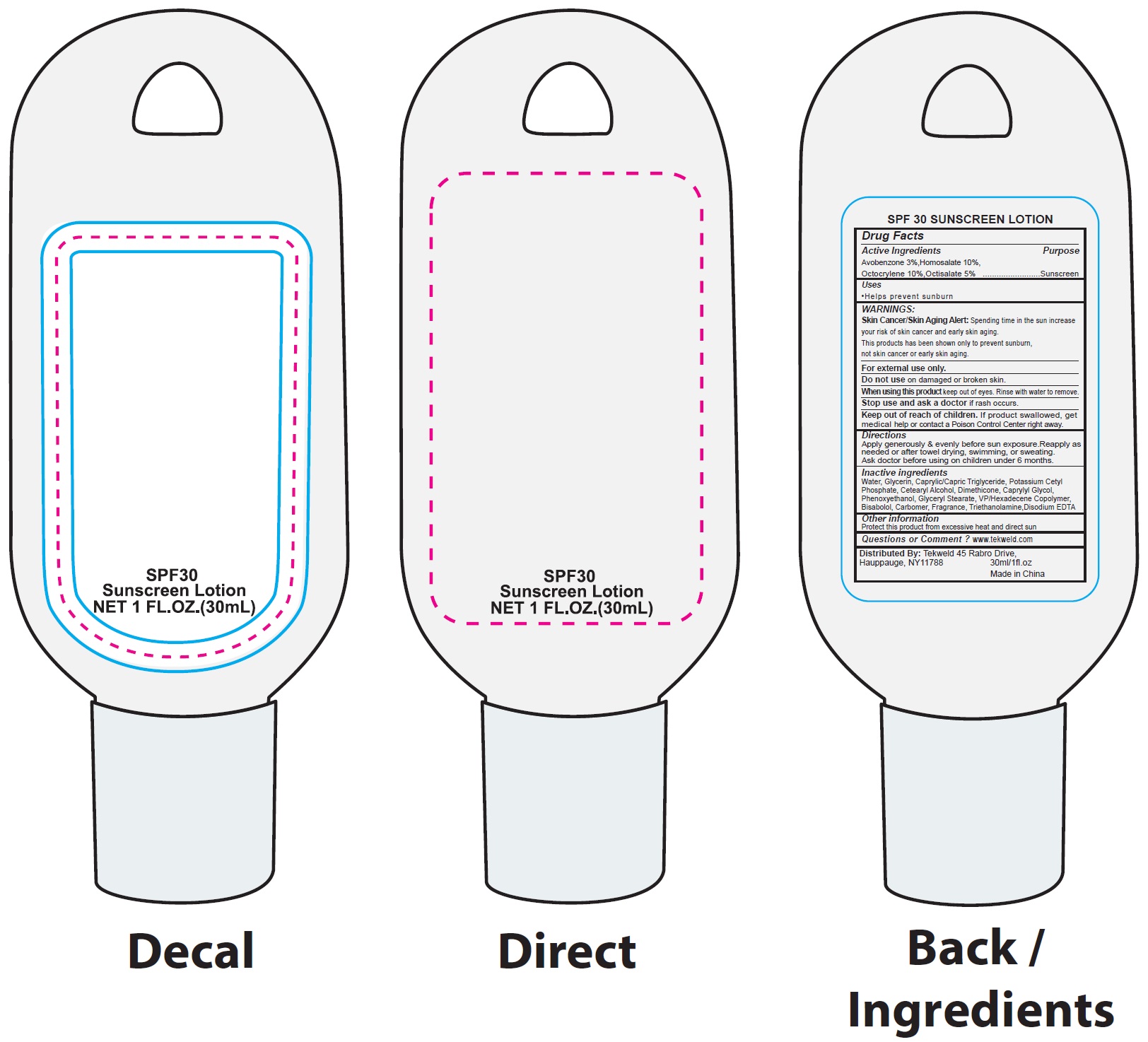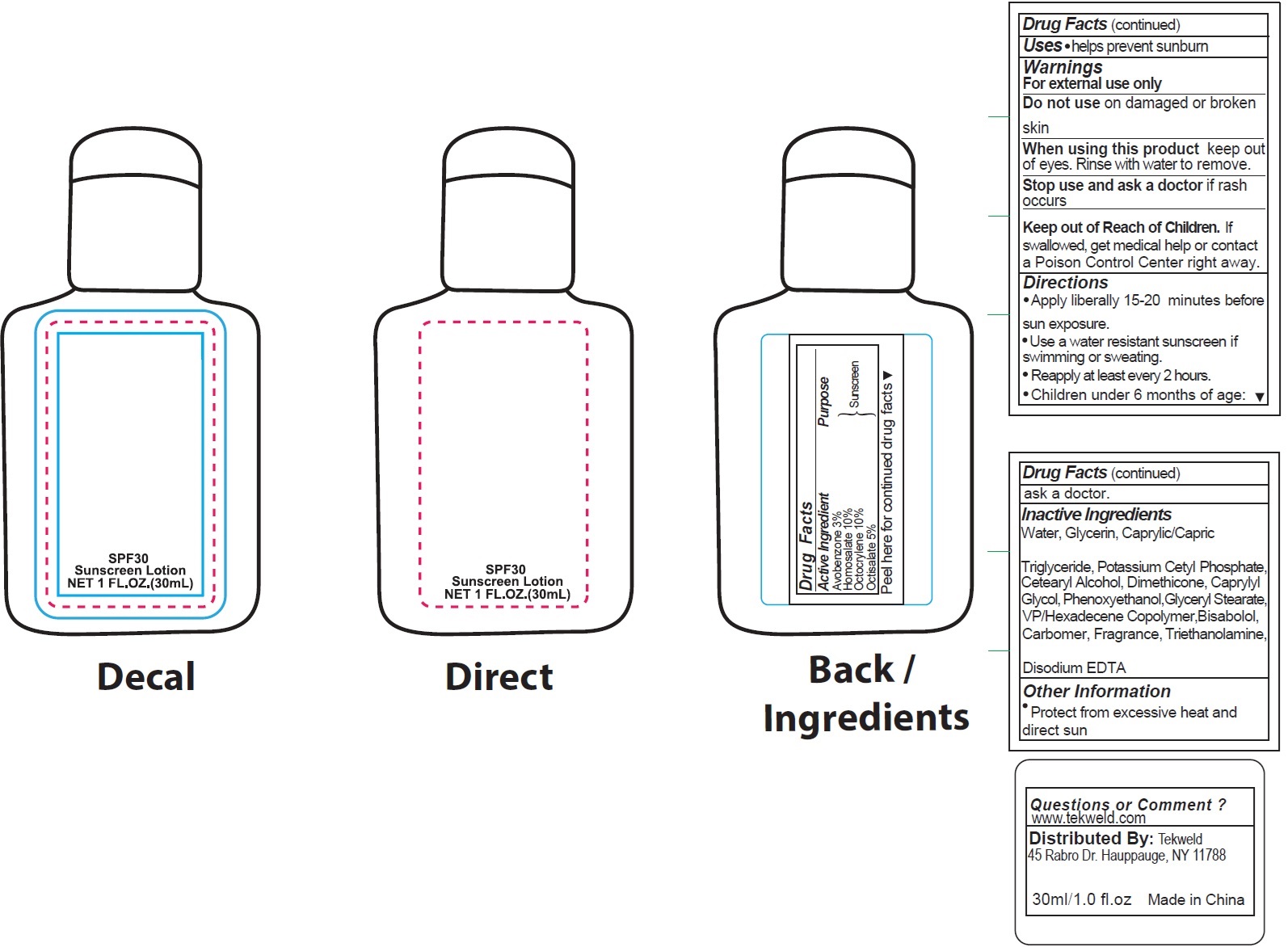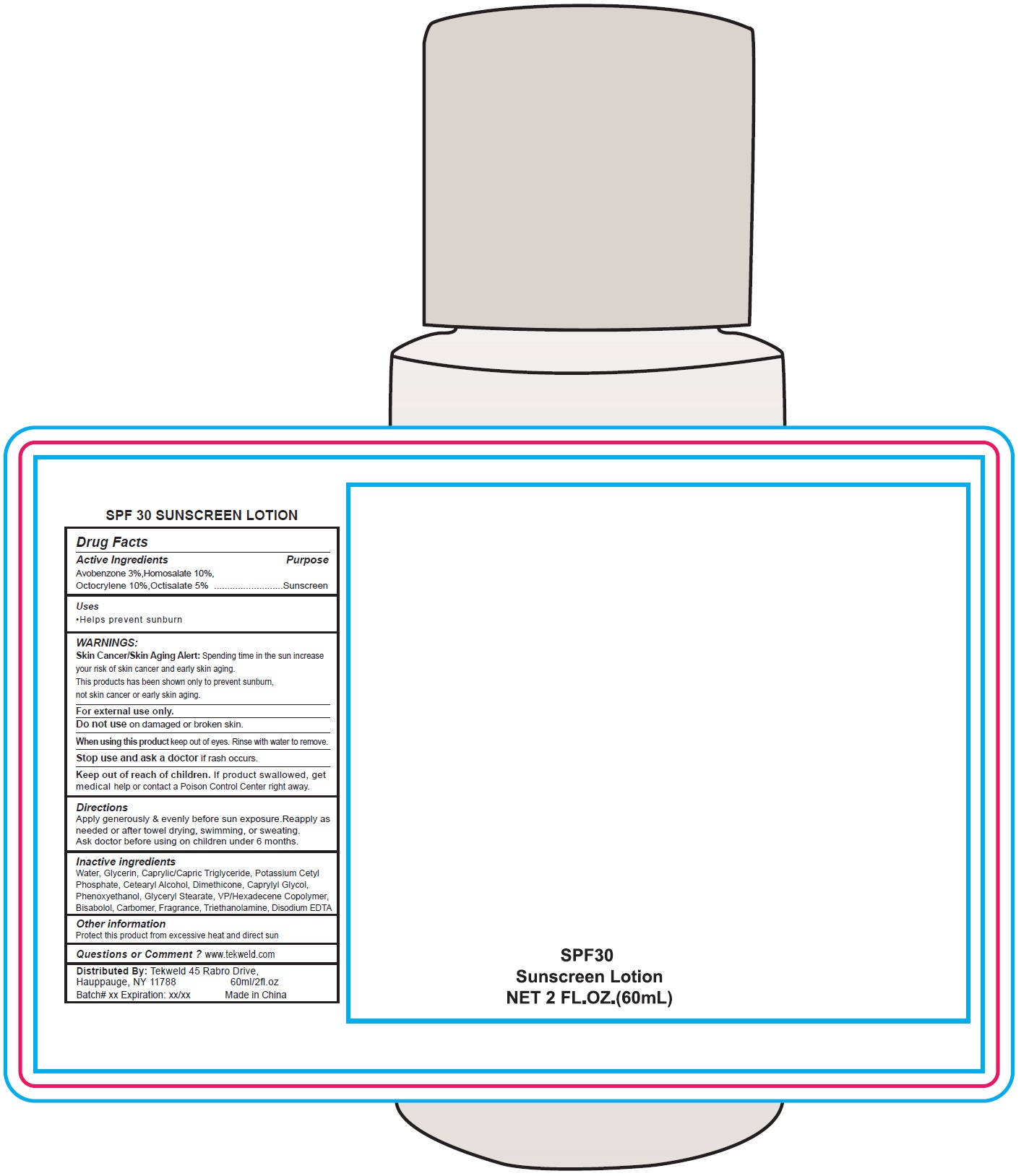 DRUG LABEL: SPF 30 Sunscreen
NDC: 71160-331 | Form: LOTION
Manufacturer: Tekweld Solutions, Inc.
Category: otc | Type: HUMAN OTC DRUG LABEL
Date: 20231226

ACTIVE INGREDIENTS: AVOBENZONE 30 mg/1 mL; HOMOSALATE 100 mg/1 mL; OCTOCRYLENE 100 mg/1 mL; OCTISALATE 50 mg/1 mL
INACTIVE INGREDIENTS: WATER; GLYCERIN; MEDIUM-CHAIN TRIGLYCERIDES; POTASSIUM CETYL PHOSPHATE; CETOSTEARYL ALCOHOL; DIMETHICONE; CAPRYLYL GLYCOL; PHENOXYETHANOL; GLYCERYL MONOSTEARATE; VINYLPYRROLIDONE/HEXADECENE COPOLYMER; LEVOMENOL; CARBOMER HOMOPOLYMER, UNSPECIFIED TYPE; TROLAMINE; EDETATE DISODIUM ANHYDROUS

SPF 30 Sunscreen Lotion

Active Ingredients

Avobenzone 3%

Homosalate 10%

Octocrylene 10%

Octisalate 5%

Purpose

Sunscreen

Uses

- Helps prevent sunburn

WARNINGS:

Skin Cancer/Skin Aging Alert:Spending time in the sun increase your risk of skin cancer and early skin aging.

This products has been shown only to prevent sunburn, not skin cancer or early skin aging.

For external use only.

Do not use

on damaged or broken skin.

When using this product

keep out of eyes. Rinse with water to remove.

Stop use and ask a doctor

if rash occurs.

Keep out of reach of children.

If product swallowed, get medical help or contact a Poison Control Center right away.

Directions

Apply generously & evenly before sun exposure.Reapply as needed or after towel drying, swimming, or sweating. Ask doctor before using on children under 6 months.

Inactive ingredients

Water, Glycerin, Caprylic/Capric Triglyceride, Potassium Cetyl Phosphate, Cetearyl Alcohol, Dimethicone, Caprylyl Glycol, Phenoxyethanol, Glyceryl Stearate, VP/Hexadecene Copolymer, Bisabolol, Carbomer, Fragrance, Triethanolamine,Disodium EDTA

Other information

Protect this product from excessive heat and direct sun

Questions or Comment ?

www.tekweld.com